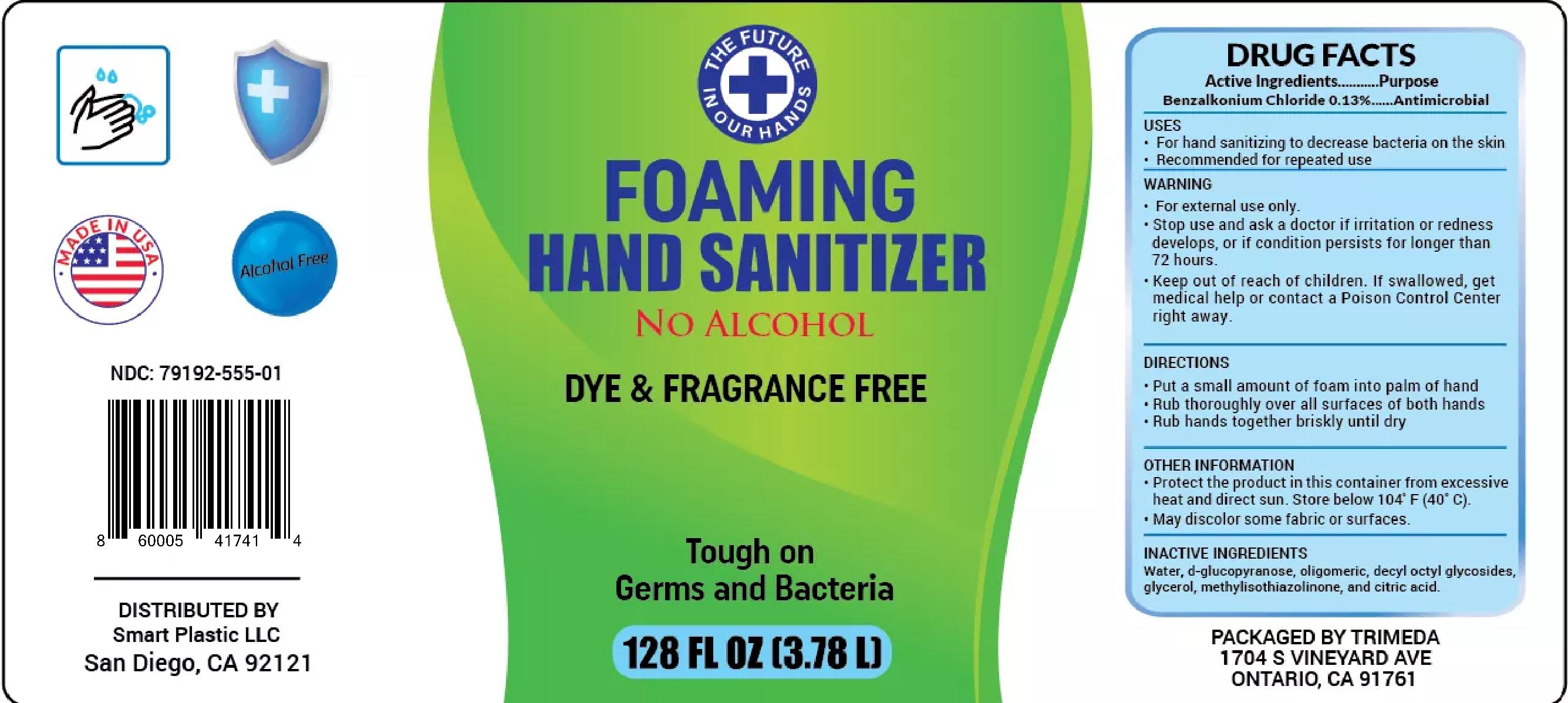 DRUG LABEL: Smart Hand Sanitizer
NDC: 79192-555 | Form: LIQUID
Manufacturer: Smart Plastic
Category: otc | Type: HUMAN OTC DRUG LABEL
Date: 20200922

ACTIVE INGREDIENTS: BENZALKONIUM CHLORIDE 0.0013 mg/1 mL
INACTIVE INGREDIENTS: CAPRYL OLIGOGLUCOSIDE; GLYCERIN; WATER; 2,3 DI-O-METHYL-D-GLUCOSE; METHYLISOTHIAZOLINONE; CITRIC ACID MONOHYDRATE

no alcohol

dye and fragrance free

tough on germs and bacteria

Smart Plastic

San Diego, CA 92121

WARNING

KEEP OUT OF REACH OF CHILDREN.

MAY BE HARMFUL IF SWALLOWED.

MAY CAUSE EYE IRRITATION.

SEE BACK PANEL FOR ADDITIONAL PRECAUTIONS AND FIRST AID.

institutional & commercial hand Sanitizer

MFG By: Chemcor Chemical Corporation

13770 Benson Avenue, Chino, CA 91710

1877- CHEMCOR

www.ChemcorChemical.com

Before discarding container, rinse with water.

For institutional and commercial use.

Active Ingredient(s)

Benzalkonium Chloride 0.13%

Purpose

Antimicrobial

Use

- For hand sanitizing to decrease bacteria on the skin
- Recommended for repeated use

Warnings

For external use only

When using this product avoid contact with eyes. In case of eye contact, flush eyes with water.

Stop use and ask a doctor if irritation or redness develops, or if condition persists for more than 72 hours.

Keep out of reach of children. If swallowed, get medical help or contact a Poison Control Center right away.

Directions

- Pump a small amount of foam into palm of hand
- Rub thoroughly over all surfaces of both hands
- Rub hands together briskly until dry

Inactive Ingredients

Water, d-glucopyranose, oligomeric, decyl octyl glycosides, glycerol, methylisothiazolinone and citric acid

Keep out of reach of children

If swallowed, get medical help or contact a Poison Control Center right away.

Packaging

3785mL NDC: 79192-555-01